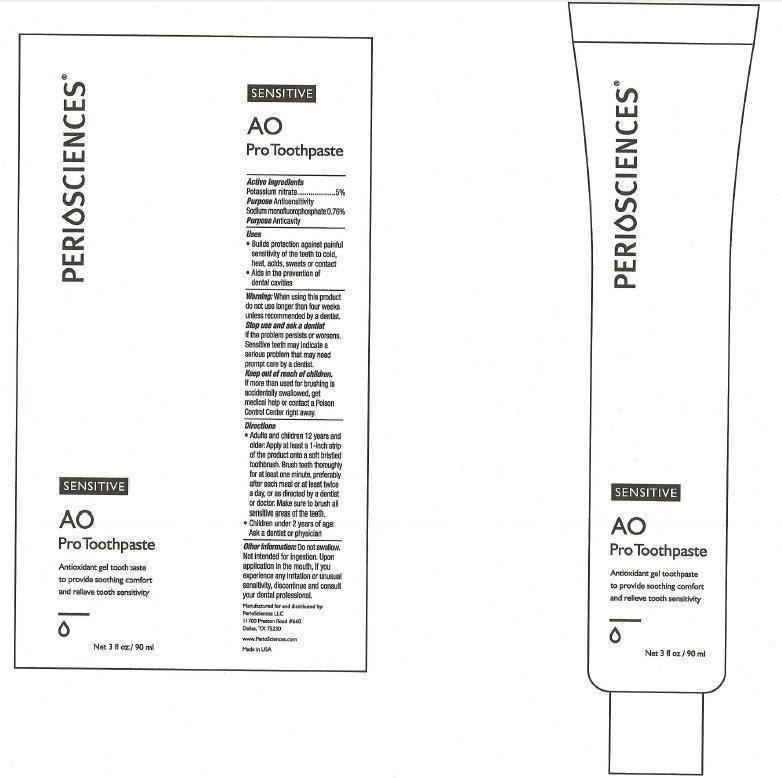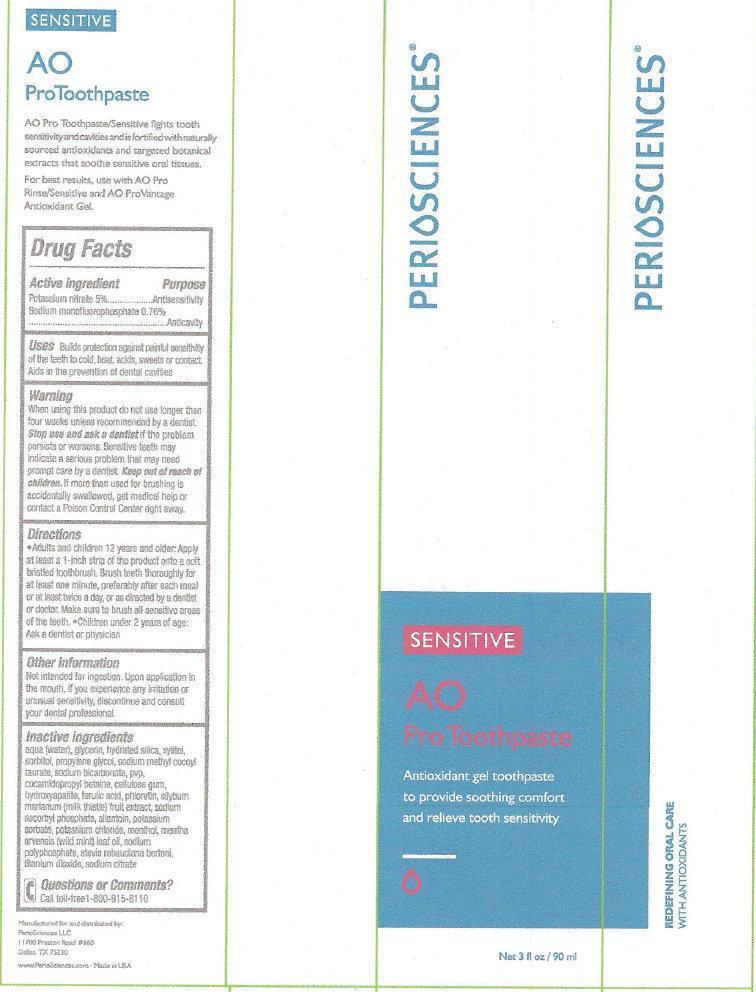 DRUG LABEL: PERIOSCIENCES SENSITIVE AO Pro
NDC: 53238-002 | Form: PASTE, DENTIFRICE
Manufacturer: PERIOSCIENCES LLC
Category: otc | Type: HUMAN OTC DRUG LABEL
Date: 20260209

ACTIVE INGREDIENTS: POTASSIUM NITRATE 50 mg/1 mL; SODIUM MONOFLUOROPHOSPHATE 1.3 mg/1 mL
INACTIVE INGREDIENTS: WATER; GLYCERIN; HYDRATED SILICA; XYLITOL; SORBITOL; PROPYLENE GLYCOL; SODIUM METHYL COCOYL TAURATE; SODIUM BICARBONATE; COCAMIDOPROPYL BETAINE; CARBOXYMETHYLCELLULOSE SODIUM; TRIBASIC CALCIUM PHOSPHATE; FERULIC ACID; PHLORETIN; SODIUM ASCORBYL PHOSPHATE; ALLANTOIN; POTASSIUM SORBATE; POTASSIUM CHLORIDE; MENTHOL; SODIUM POLYMETAPHOSPHATE; TITANIUM DIOXIDE; SODIUM CITRATE

PERIOSCIENCES SENSITIVE AO ProToothpaste

Active ingredient

Potassium nitrate 5%
Sodium monofluorophosphate 0.76%

Purpose

Antisensitivity
Anticavity

Uses

Builds protection against painful sensitivity of the teeth to cold, heat, acids, sweets or contact. Aids in the prevention of dental cavities

Warning

When using this product

do not use longer than four weeks unless recommended by a dentist.

Stop use and ask a dentist

if the problem persists or worsens. Sensitive teeth may indicate a serious problem that may need prompt care by a dentist.

Keep out of reach of children.

If more than used for brushing is accidentally swallowed, get medical help or contact a Poison Control Center right away.

Directions

- Adults and children 12 years of age and older: Apply at least a 1-inch strip of the product onto a soft bristled toothbrush. Brush teeth thoroughly for at least one minute, preferably after each meal or at least twice a day, or as directed by a dentist or doctor. Make sure to brush all sensitive areas of the teeth.
- Children under 2 years of age: Ask a dentist or physician

Other information

Not intended for ingestion. Upon application in the mouth, if you experience any irritation or unusual sensitivity, discontinue and consult your dental professional.

Inactive ingredients

aqua (water), glycerin, hydrated silica, xylitol, sorbitol, propylene glycol, sodium methyl cocoyl taurate, sodium bicarbonate, pvp, cocamidopropyl betaine, cellulose gum, hydroxyapatite, ferulic acid, phloretin, silyburn marianum (milk thistle) fruit extract, sodium ascorbyl phosphate, allantoin, potassium sorbate, potassium chloride, menthol, mentha arvensis (wild mint) leaf oil, sodium polyphosphate, stevia rebaudiana bertoni, titanium dioxide, sodium citrate

Questions or Comments?

Call toll-free 1-800-915-8110

SENSITIVE AO ProToothpaste

AO Pro Toothpaste/Sensitive fight tooth sensitivity and cavities and is fortified with naturally sourced antioxidants and targeted botanical extracts that soothe sensitive oral tissues.
For best results, use with AO ProRinse/Sensitive and AO ProVantage Antioxidant Gel.
Manufactured and distributed by:
Periosciences
LLC
11700 Preston Road #660
Dallas, TX 75230
www.PerioSciences.com - Made in USA

PACKAGE LABEL

PERIOSCIENCES SENSITIVE AO ProToothpaste Antioxidant gel toothpaste to provide soothing comfort and relieve tooth sensitivity Net 3 fl oz / 90 ml REDEFINING ORAL CARE WITH ANTIOXIDANTS